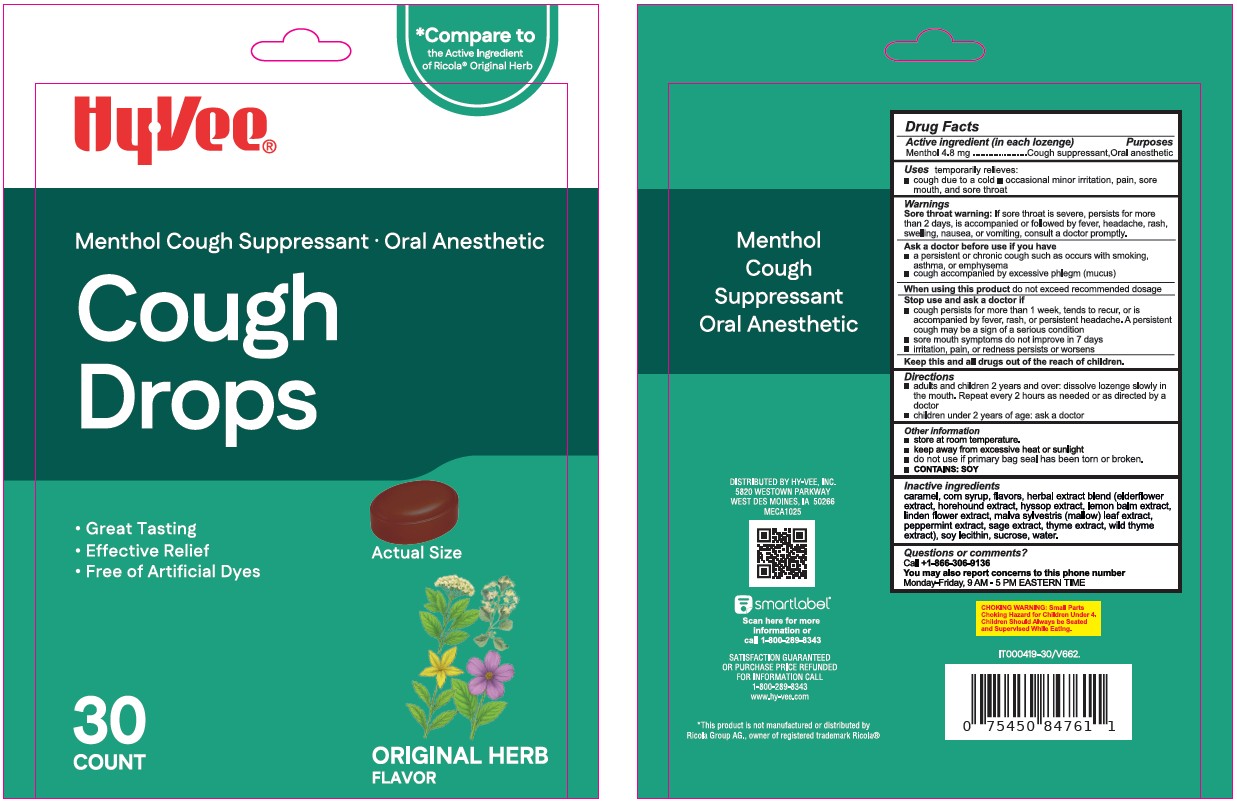 DRUG LABEL: HyVee Cough Drops Original Herb
NDC: 42507-906 | Form: LOZENGE
Manufacturer: HY-VEE, INC
Category: otc | Type: HUMAN OTC DRUG LABEL
Date: 20260109

ACTIVE INGREDIENTS: MENTHOL 4.8 mg/1 1
INACTIVE INGREDIENTS: CARAMEL; CORN SYRUP; SAMBUCUS NIGRA FLOWER; HOREHOUND; HYSSOPUS OFFICINALIS FLOWERING TOP; LEMON BALM OIL; TILIA CORDATA FLOWER; MALVA SYLVESTRIS LEAF; PEPPERMINT; SAGE; THYME; WILD THYME; LECITHIN, SOYBEAN; SUCROSE; WATER

Xiamen-Hyvee Cough Drops Original Herb 30

Active Ingredient(s)

Menthol 4.8 mg

Purpose

Purposes cough suppressant, oral anesthetic

Use

temporary relieves: ■ cough due to cold ■ occasional minor irritation or sore throat

Warnings

Sore throat warning: If sore throat is severe, persists for more than 2 days, is accompanied or follow headache, rash, swelling, nausea, or vomiting, consult a doctor promptly.

Ask a doctor before use if you have: ■ persistent or chronic cough such as occurs with smoking, asthma, or emphysema ■ cough accompanied by excessive phlegm (mucus).

Stop use and ask a doctor if ■ cough persists for more than 1 week, tends to recur, or is accompained by fever, rash, or persistent headache. These could be signs of a serius condition. ■ sore mouth does not improve in 7 days ■ irritation, pain, or redness persists or worsens.

KEEP OUT OF REACH OF CHILDREN

Keep this and all drugs out of reach of children

Directions

■ adults and children 2 years and over: dissolve lozenge slowly in the mouth. Repeat every 2 hours as needed or directed by doctor.

■ children under 2 years: ask a doctor.

Other information

■ store at room temperature ■ Keep away from excessive heat or sunlight ■ do not use if primary bag seal has been torn or broken ■ contains: SOY.

Inactive ingredients

caramel, corn syrup, flavors, herbal extract blend (elderflower extract, horehound extract, hyssop extract, lemon balm extract, linden flower extract, malva sylvestris (mallow) leaf extract, peppermint extract, sage extract, thyme extract, wild thyme extract), SOY LECHITIN, sucrose, water

QUESTIONS

Call +1-866-306-9136

You may also report concerns to this phone number

Monday to Friday, 9 AM - 5 PM Eastern Time